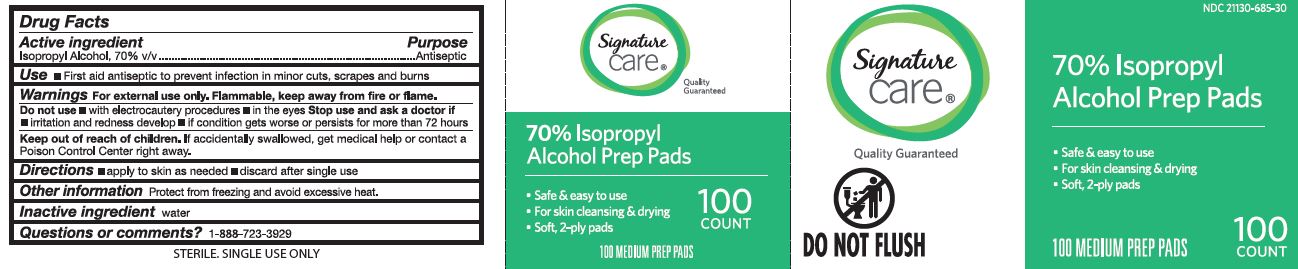 DRUG LABEL: Signature Care Alcohol Prep Pad
NDC: 21130-685 | Form: CLOTH
Manufacturer: Better Living Brands LLC
Category: otc | Type: HUMAN OTC DRUG LABEL
Date: 20250103

ACTIVE INGREDIENTS: ISOPROPYL ALCOHOL 70 mL/100 mL
INACTIVE INGREDIENTS: WATER

21130-685 Signiture Care IPA pads

Active ingredient

Isopropyl alcohol 70% v/v

Purpose

Antiseptic

Uses

- • first aid antiseptic to prevent infection in minor cuts, scrapes and burns

Warnings

- For external use only.
- Flammable, keep away from fire or flame.

Do not use

- • with electrocautery procedures
- • longer than 1 week unless directed by a doctor

When using this product

- • do not get into eyes
- • do not apply over large areas of the body
- • in case of deep or puncture wounds, animal bites or serious burns, consult a doctor

Stop use and ask a doctor if

- • irritation or redness develop
- • condition gets worse or persists for more than 72 hours

Keep out of reach of children.

If accidentally swallowed, get medical help or contact a Poison Control Center right away.

Directions

- • apply to skin as needed
- • discard after single use

Other information

- • protect from freezing and avoid excessive heat
- • not made with natural rubber latex

Inactive ingredients

water

Manufacturing Information

Distributed by:

Better Living Brands LLC

P.O. Box 99, Pleasanton, CA 94566 USA

Packaged in China with components of Taiwan

1-888-723-3929

www.betterlivingbrandsLLC.com

REF: SAF090737V2

V2 RH22SXM